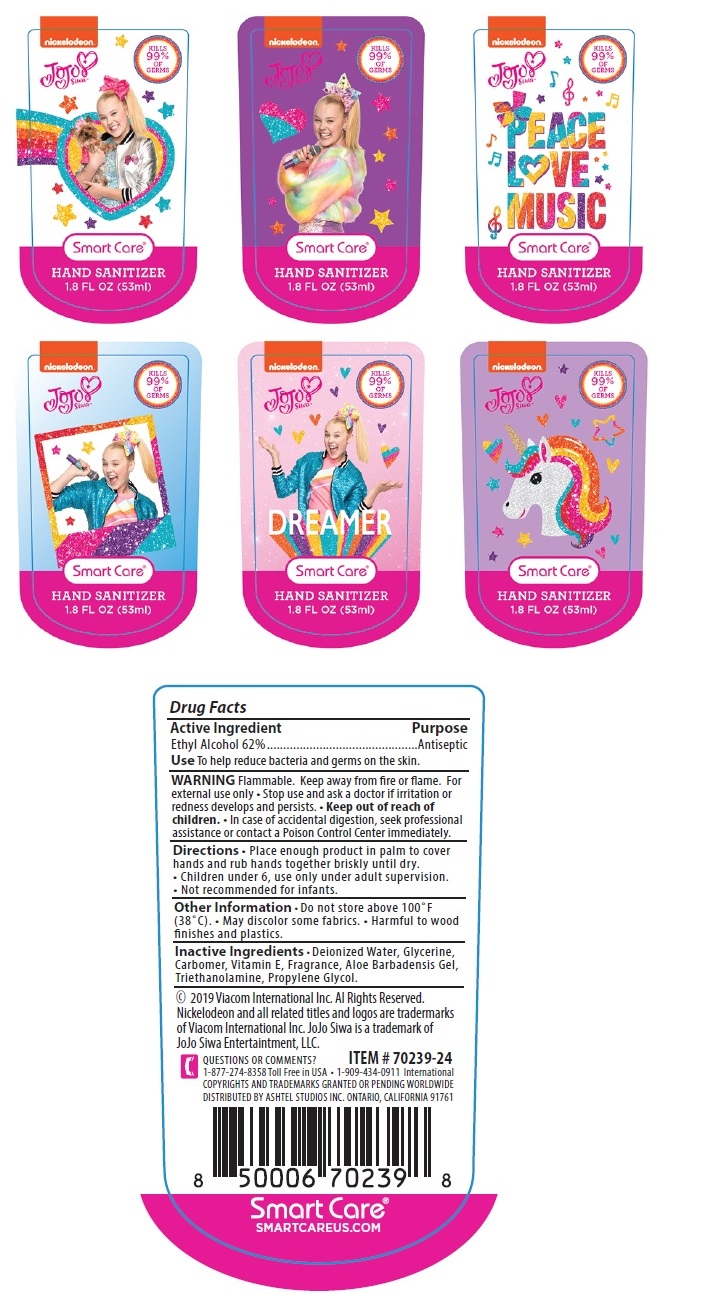 DRUG LABEL: JOJO Siwa HAND SANITIZER
NDC: 72922-004 | Form: GEL
Manufacturer: ShangRao chunyu Technology CO.,LTD.
Category: otc | Type: HUMAN OTC DRUG LABEL
Date: 20200709

ACTIVE INGREDIENTS: ALCOHOL 62 mL/100 mL
INACTIVE INGREDIENTS: WATER; GLYCERIN; CARBOMER HOMOPOLYMER, UNSPECIFIED TYPE; .ALPHA.-TOCOPHEROL; ALOE VERA LEAF; TROLAMINE; PROPYLENE GLYCOL

Smart Care® Hand Sanitizer

Active Ingredient

Ethyl Alcohol 62%

Purpose

Antiseptic

Use

To help reduce bacteria and germs on the skin.

WARNING

Flammable. Keep away from fre or flame. For external use only • Stop use and ask a doctor if irritation or redness develops and persists.

• Keep out of reach of children. • In case of accidental digestion, seek professional assistance or contact a Poison Control Center immediately.

Directions

• Place enough product in palm to cover hands and rub hands together briskly until dry.
• Children under 6, use only under adult supervision.
• Not recommended for infants.

Other information

• Do not store above 100 °F (38 °C). • May discolor some fabrics. • Harmful to wood fnishes and plastics.

Inactive Ingredients

• Deionized Water, Glycerine, Carbomer, Vitamin E, Fragrance, Aloe Barbadensis Gel, Triethanolamine, Propylene Glycol.

KILLS 99% OF GERMS

Smart Care®

© 2019 Viacom International Inc. Al Rights Reserved.
Nickelodeon and all related titles and logos are tradermarks of Viacom International Inc. JoJo Siwa is a trademark of JoJo Siwa Entertaintment, LLC.

QUESTIONS OR COMMENTS?
1-877-274-8358 Toll Free in USA • 1-909-434-0911 International
COPYRIGHTS AND TRADEMARKS GRANTED OR PENDING WORLDWIDE
DISTRIBUTED BY ASHTEL STUDIOS INC. ONTARIO, CALIFORNIA 91761